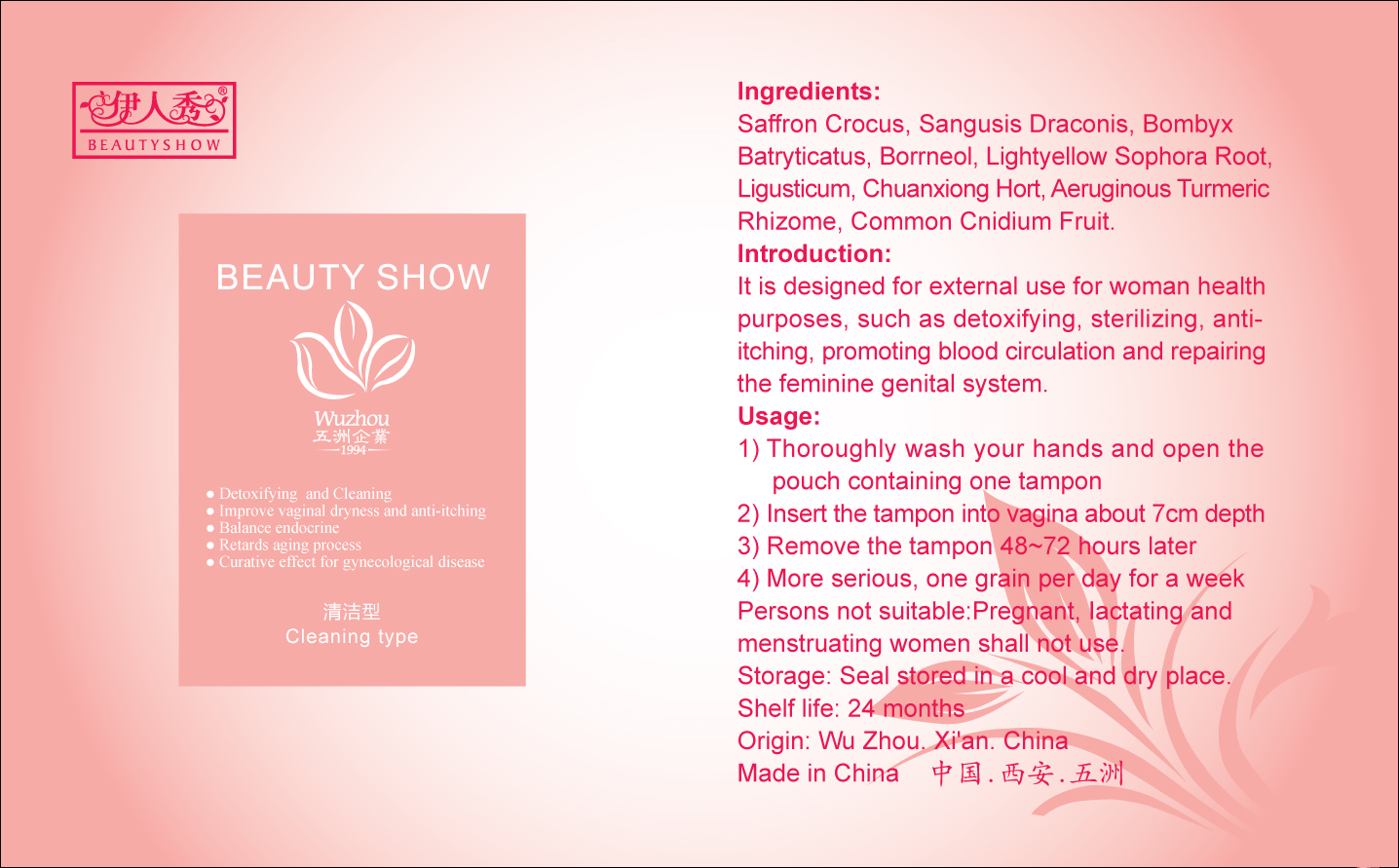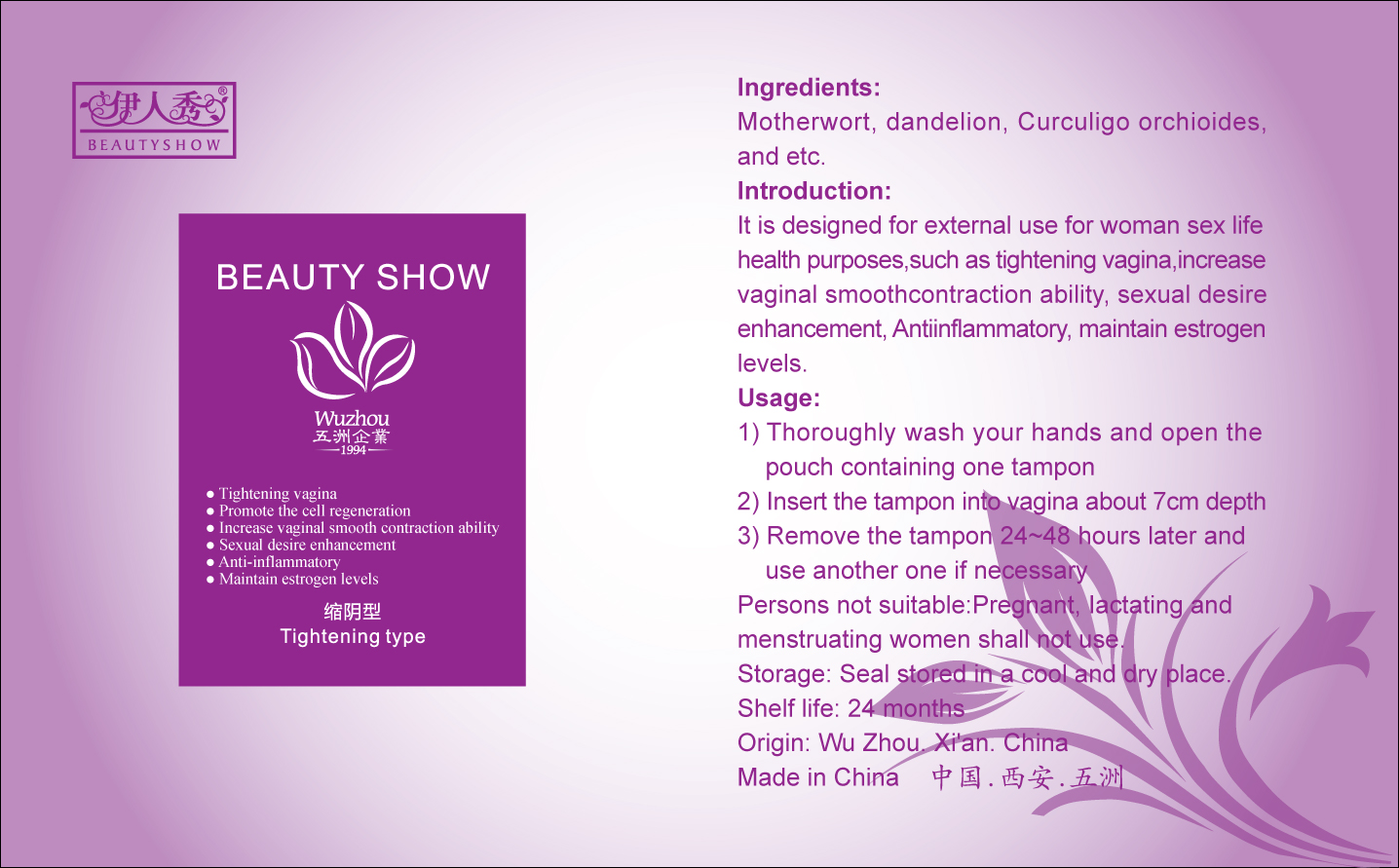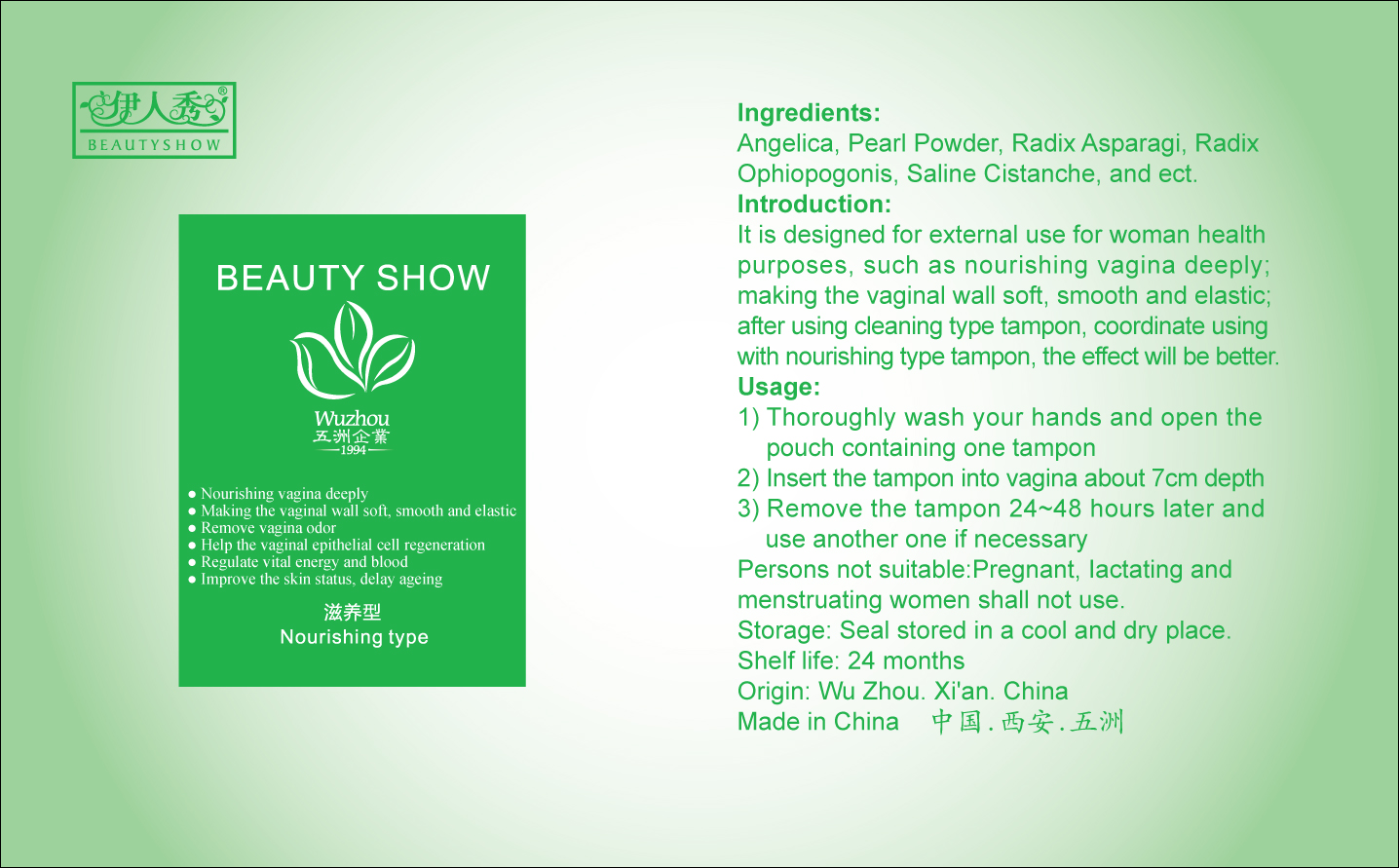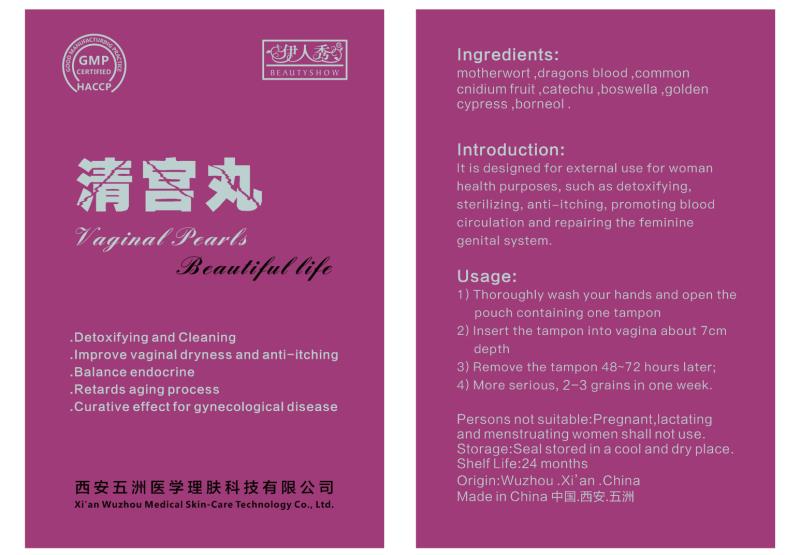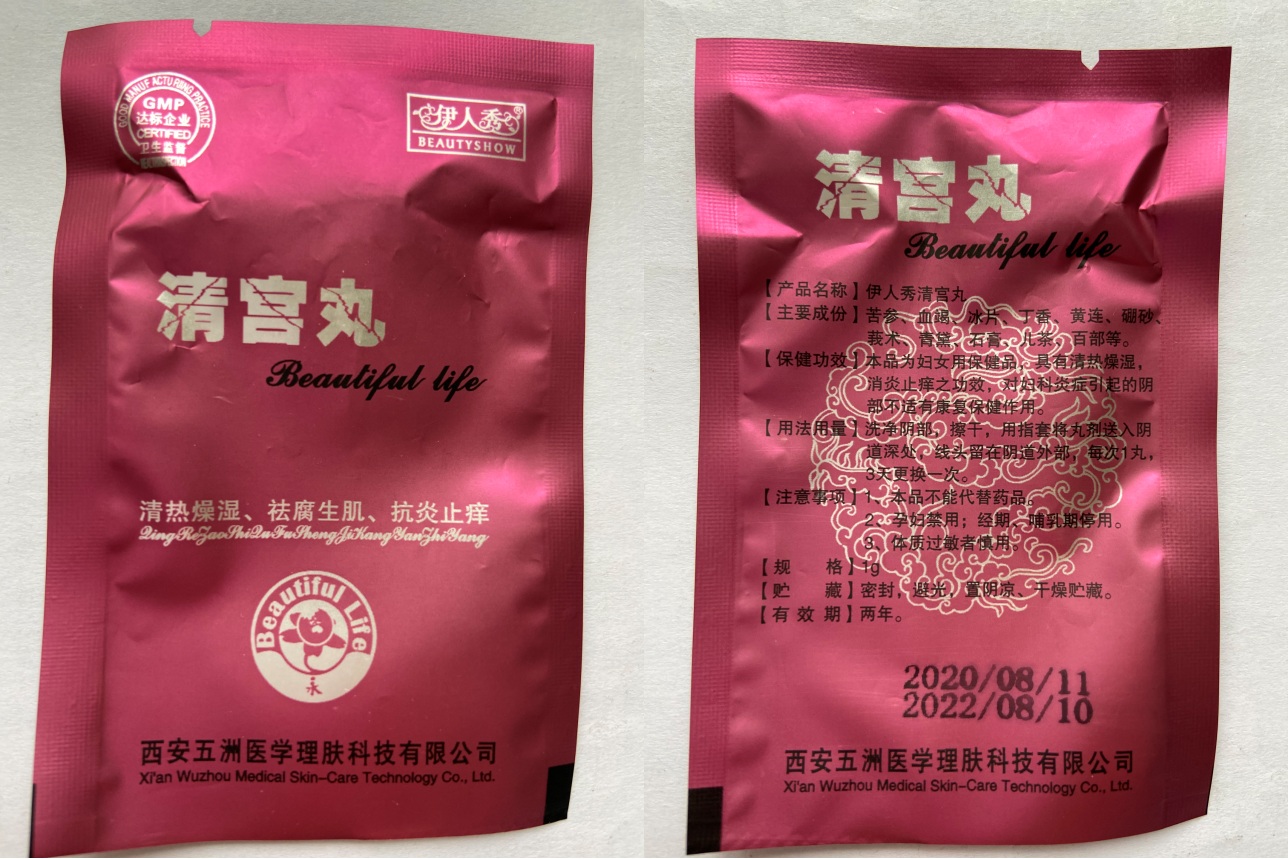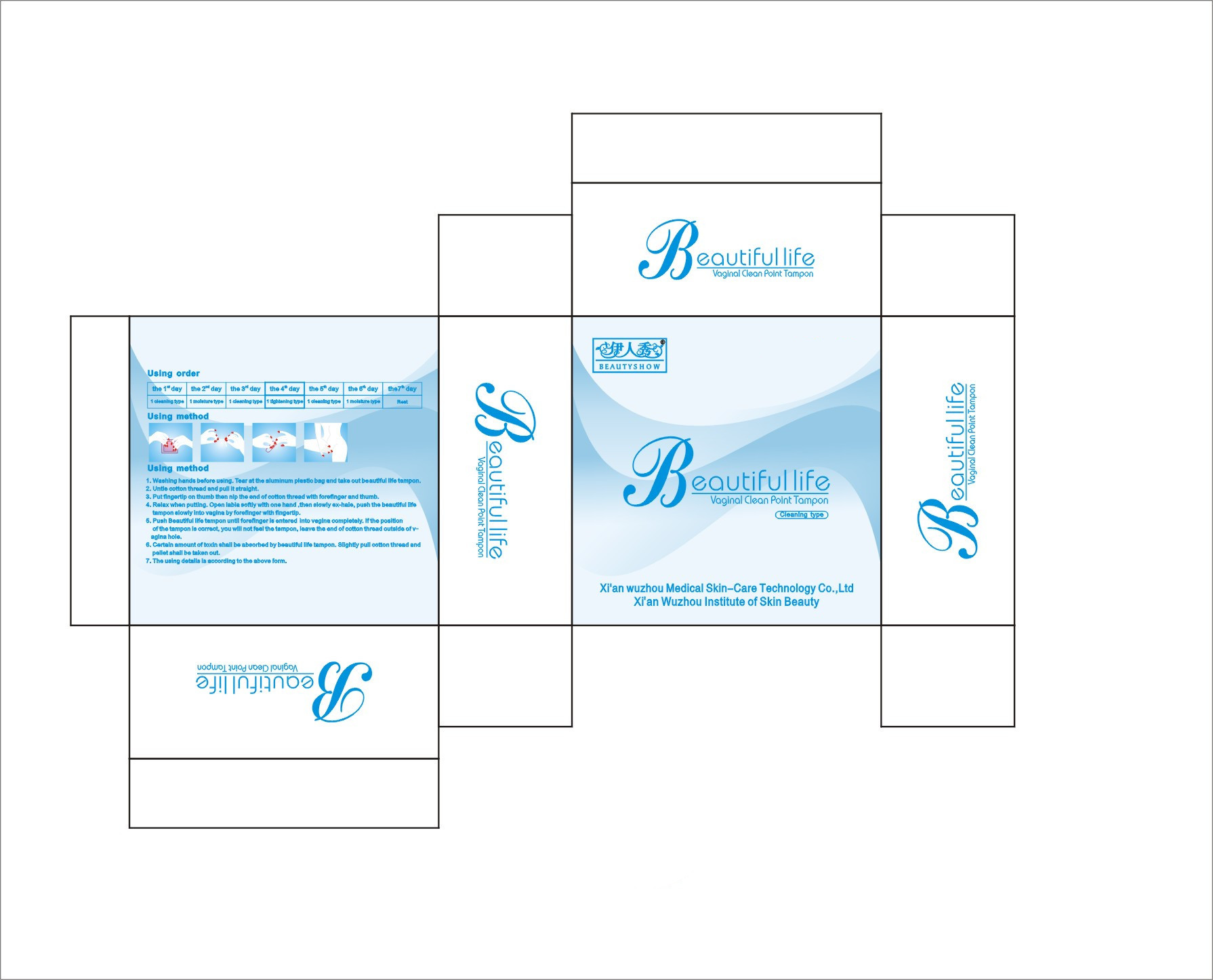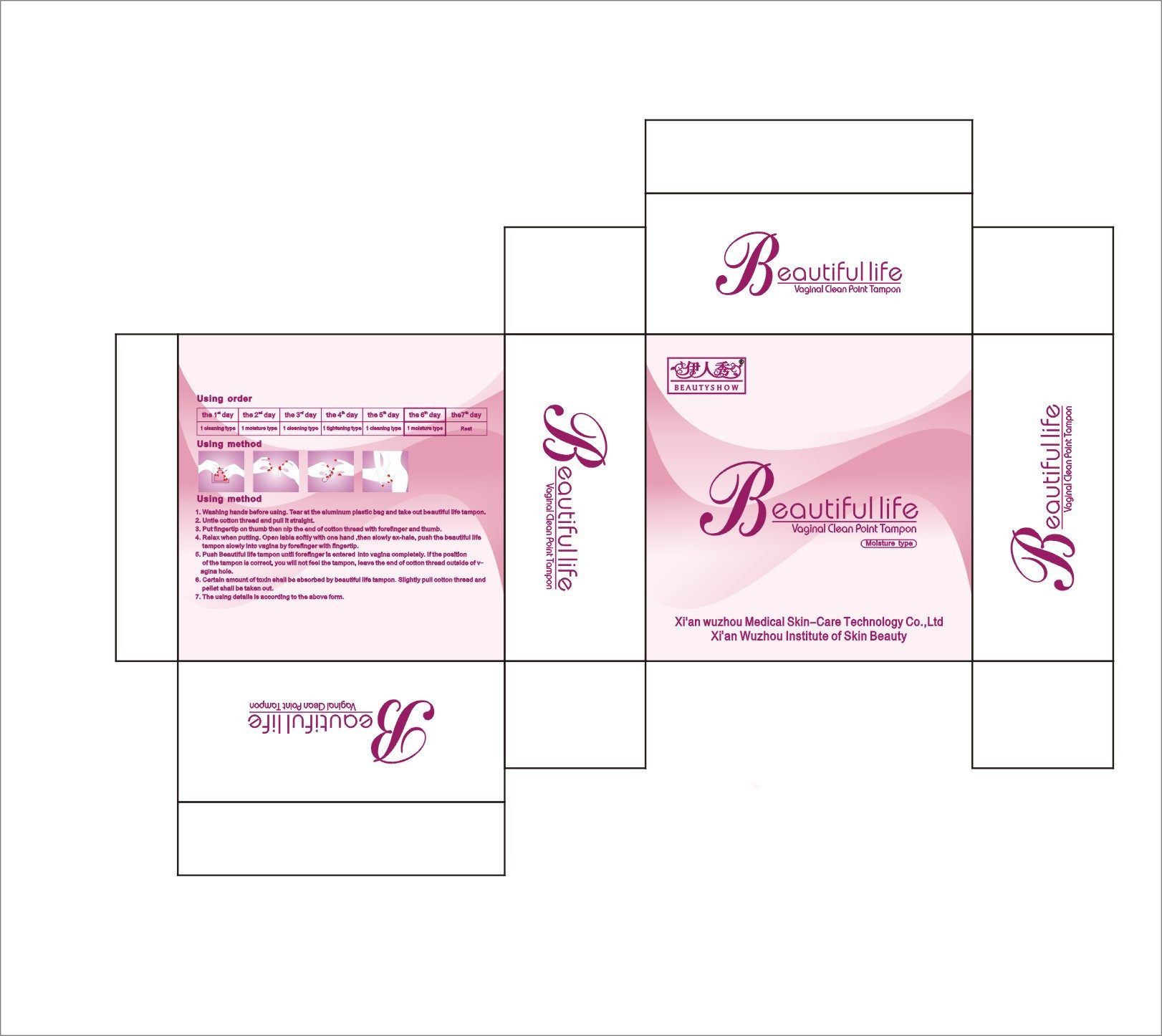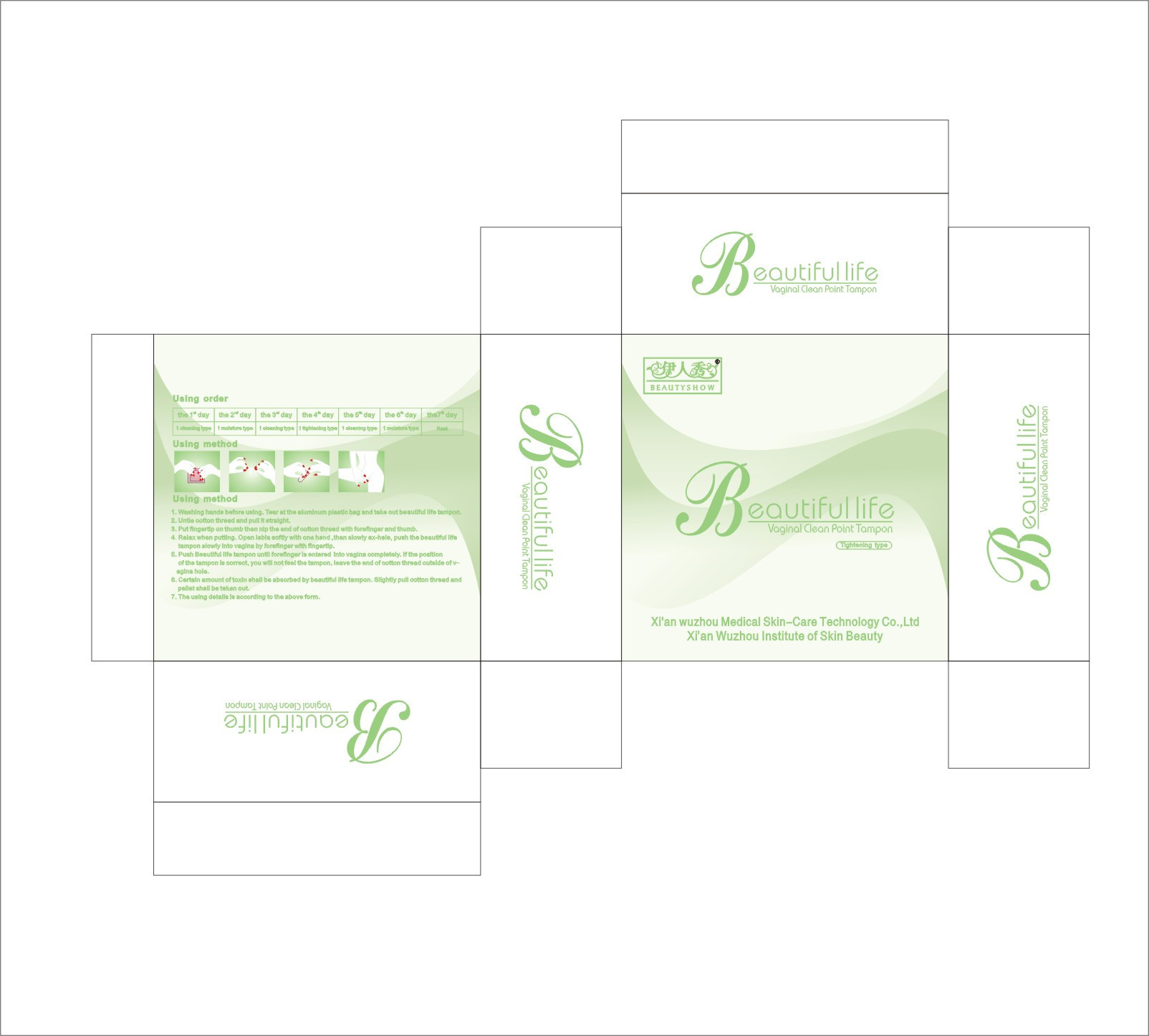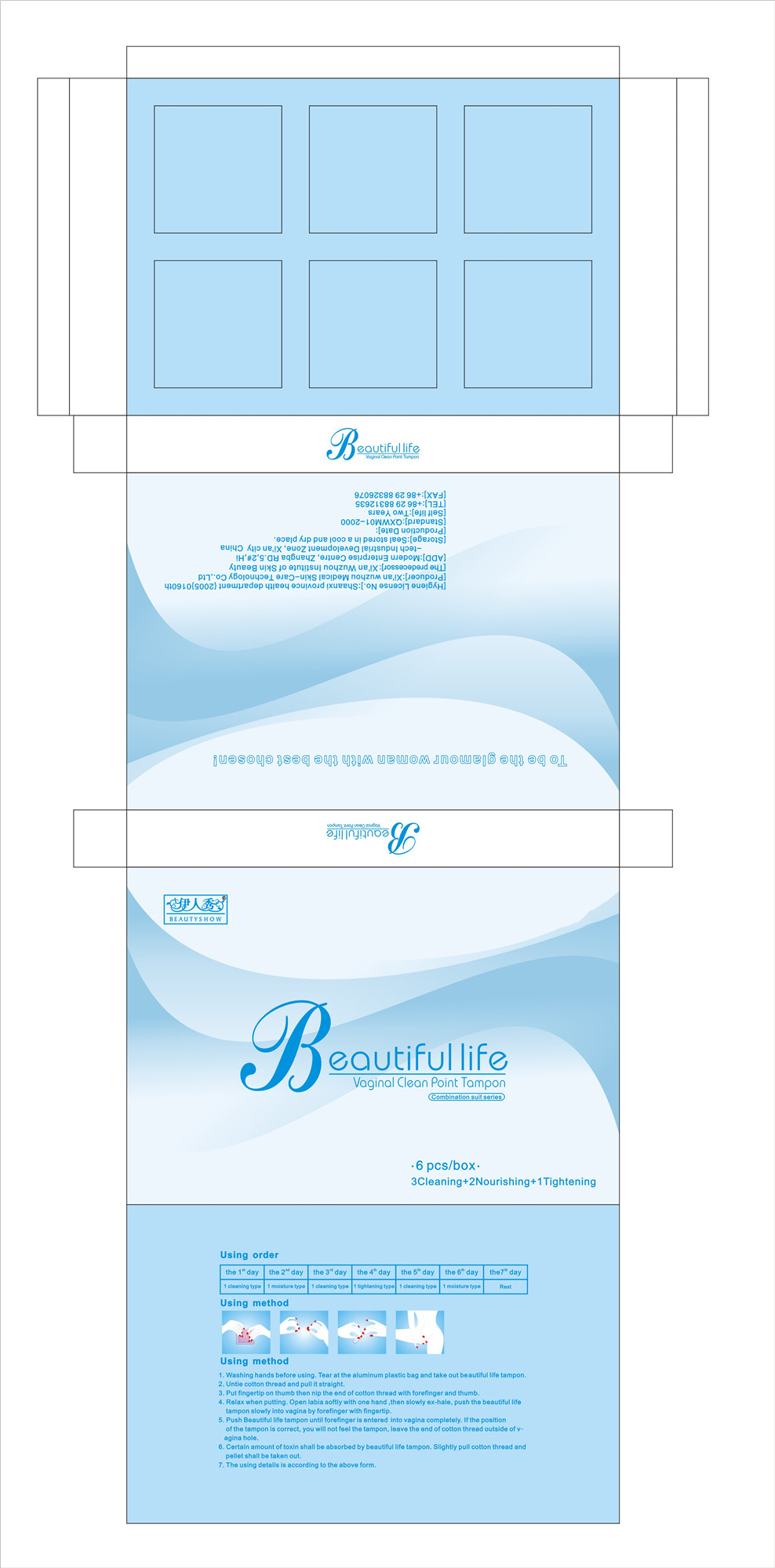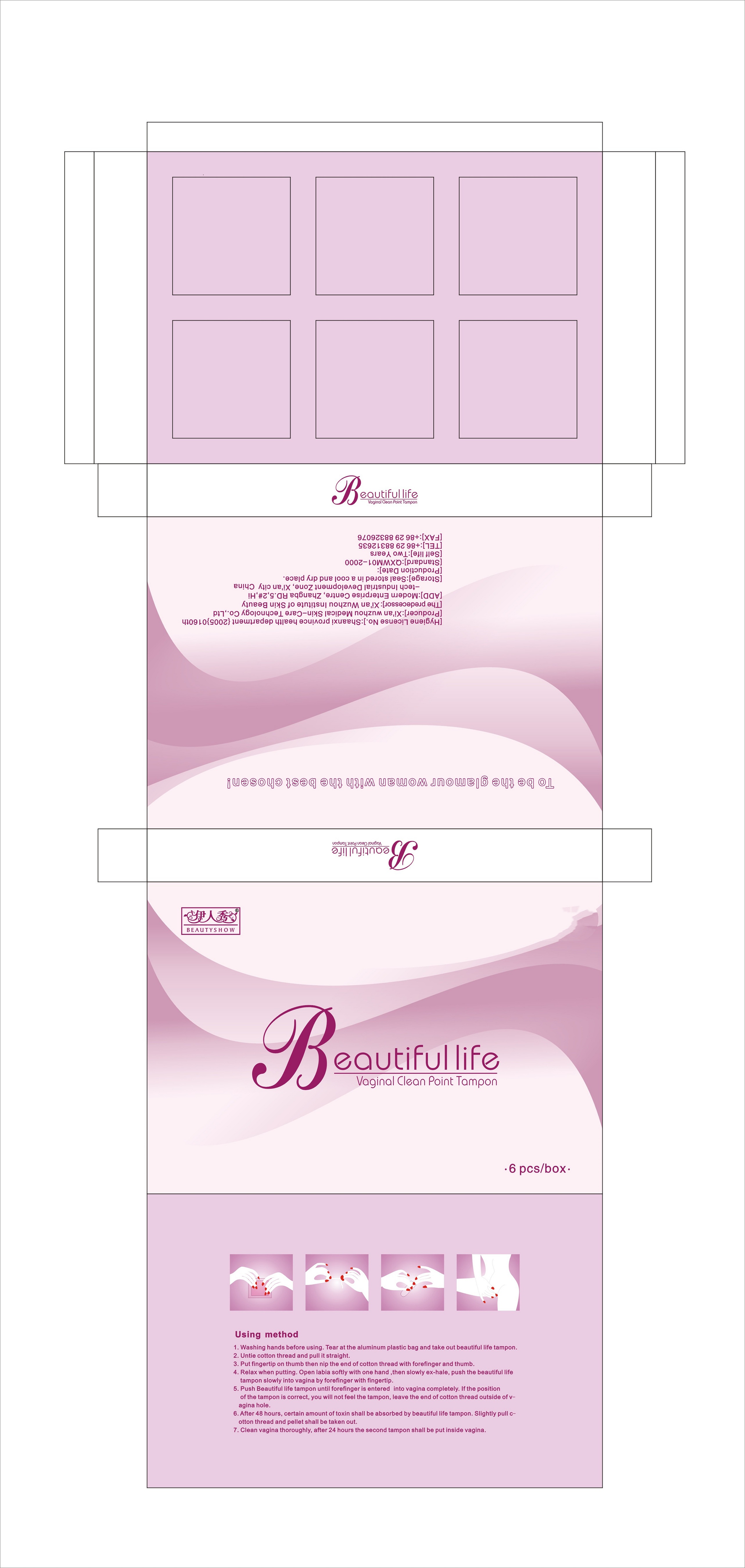 DRUG LABEL: Beauty Show Vaginal Pearls
NDC: 80093-100 | Form: SUPPOSITORY
Manufacturer: Xi'an Wuzhou Medical Skin Care Technology Co.,Ltd.
Category: otc | Type: HUMAN OTC DRUG LABEL
Date: 20201025

ACTIVE INGREDIENTS: CNIDIUM MONNIERI FRUIT 27 g/100 g
INACTIVE INGREDIENTS: DRAGON'S BLOOD; BORNEOL; LEONURUS CARDIACA WHOLE; BOSWELLIA SERRATA RESIN OIL; SENEGALIA CATECHU WOOD; PHELLODENDRON CHINENSIS BARK

WARNINGS

If irritated, use womb healing soap and womb healing salve to soothe your vagina.

Each pearl constitutes one cleanse. A Royal Flush is using up to 3 pearls at once.

ACTIVE INGREDIENT

N/A

Keep out of reach of children.

DOSAGE AND ADMINISTRATION

Feel your cervix, place pearl inside vagina next to cervix. Pearl will discharge within 7 days. Do not remove pearl.

INDICATIONS AND USAGE

Vaginal cleansing products, namely, vaginal suppositories in the nature of prearls for the purpose of relieving erosion.

PURPOSE

FROM CERVICITIS, RELIEVING SYMPTOMS OF PELVIC INFLAMMATORY DISEASE, RELIEVING MENSTRUAL IRREGULARITIES, ELIMINATING VAGINAL ODOR AND

CANDIDIASIS, AND VAGINAL TIGHTENING AND BEAUTIFICATION.

INACTIVE INGREDIENT

- DRAGON'S BLOOD
- LEONURUS CARDIACA WHOLE
- CNIDIUM MONNIERI FRUIT
- SENEGALIA CATECHU WOOD
- BOSWELLIA SERRATA RESIN OIL
- PHELLODENDRON CHINENSIS BARK
- BORNEOL